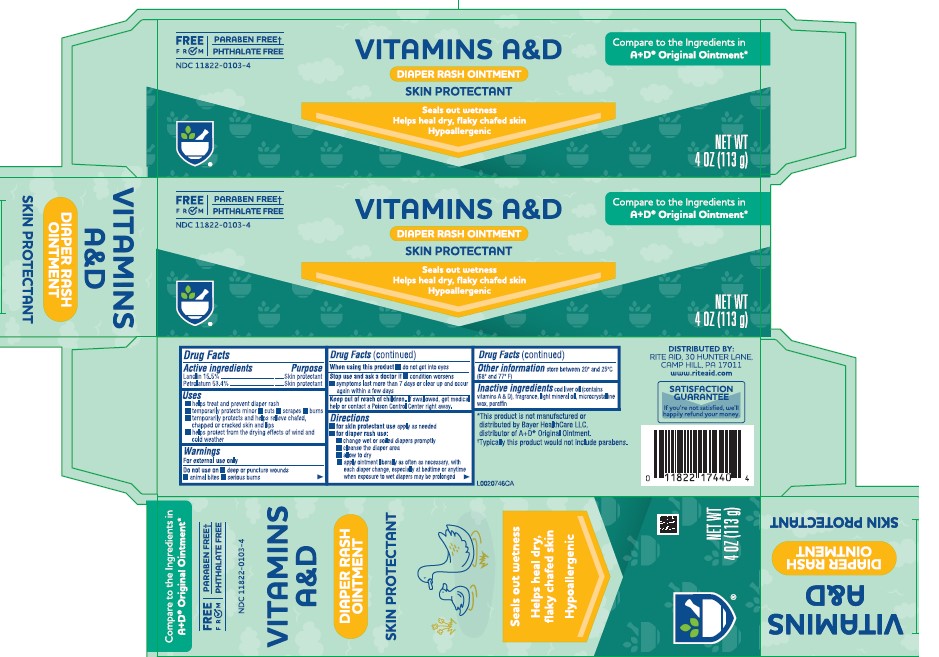 DRUG LABEL: Lanolin, Petrolatum
NDC: 11822-0103 | Form: OINTMENT
Manufacturer: Rite Aid Corporation
Category: otc | Type: HUMAN OTC DRUG LABEL
Date: 20260130

ACTIVE INGREDIENTS: LANOLIN 155 mg/1 g; PETROLATUM 534 mg/1 g
INACTIVE INGREDIENTS: COD LIVER OIL; LIGHT MINERAL OIL; MICROCRYSTALLINE WAX; PARAFFIN

Rite Aid 013.000/013AA-AB
Vitamin A&D Ointment

Active ingredients

Lanolin 15.5%

Petrolatum 53.4%

Purpose

Skin protectant

Uses

- helps treat and prevent diaper rash
- temporarily protects minor: cuts - scrapes - burns
- temporarily protects and helps relieve chafed, chapped or cracked skin and lips
- helps protect from the drying effects of wind and cold weather

Warnings

For external use only

Do not use on

- deep or puncture wounds
- animal bites
- serious burns

When using this product

- do not get into eyes

Stop use and ask a doctor if

- condition worsens
- symptoms last more than 7 days or clear up and occur again within a few days

Keep out of reach of children.

If swallowed, get medical help or contact a Poison Control Center right away.

Directions

- for skin protectant use: apply as needed
- for diaper rash use:
- change wet or soiled diapers promptly
- cleanse the diaper area
- allow to dry
- apply ointment liberally as often as necessary, with each diaper change, especially at bedtime or anytime when exposure to wet diapers may be prolonged

other information

store between 20º and 25ºC (68º and 77º F)

Inactive ingredients

cod liver oil (contains vitamins A+D), fragrance, light mineral oil, microcrystalline wax, paraffin

Disclaimer

*This product is not manufactured or distributed by Bayer HealthCare LLC, distributer of A+D®Original Ointment.

Typically this product would not include patabens.

Adverse Reaction

DISTRIBUTED BY:

RITE AID, 30 HUNTER LANE,

CAMP HILL, PA 17011

www.riteaid.com

SATISFACTION GUARANTEE

If you're not satisfied, we'll happily refund your money.

principal display panel

FREE FROM

PARABEN FREE†

PHTHALATE FREE

NDC 11822-0103-4

VITAMINS A & D

DIAPER RASH OINTMENT

SKIN PROTECTANT

Seals out wetness

Helps heal dry, flaky chafed skin

Hypoallergenic

Compare to the ingredicants in A+D®Original Ointment*

NET WT 4 oz (113 g)